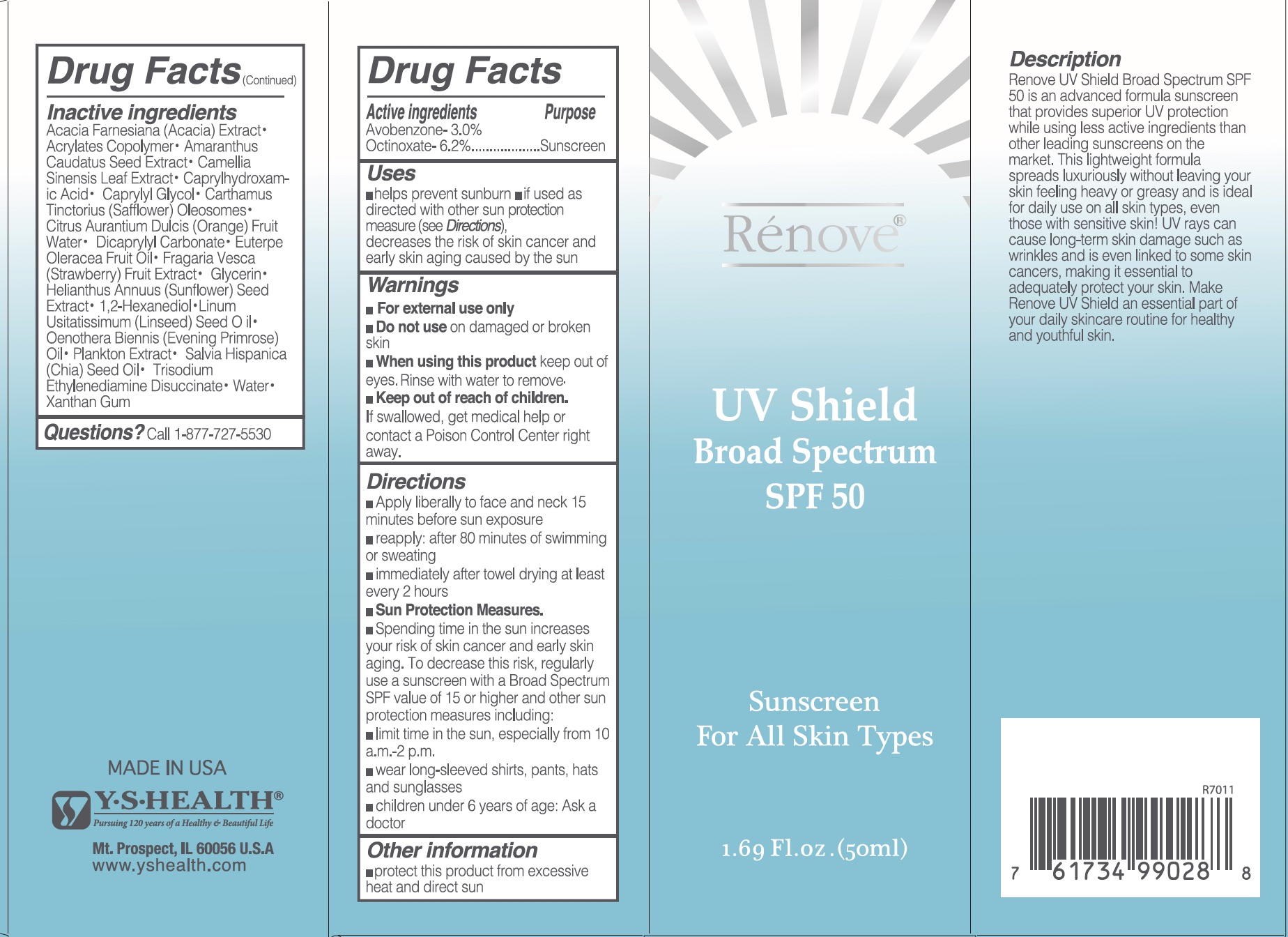 DRUG LABEL: Renove UV Shield Broad Spectrum SPF 50
NDC: 60782-003 | Form: CREAM
Manufacturer: Y.S. Health Corp.
Category: otc | Type: HUMAN OTC DRUG LABEL
Date: 20170307

ACTIVE INGREDIENTS: OCTINOXATE 6.2 g/10 mL; AVOBENZONE 3 g/10 mL
INACTIVE INGREDIENTS: ORANGE; GREEN TEA LEAF; CARTHAMUS TINCTORIUS (SAFFLOWER) OLEOSOMES; DICAPRYLYL CARBONATE; FRAGARIA VESCA FRUIT; GLYCERIN; SUNFLOWER SEED; WATER; CAPRYLHYDROXAMIC ACID; CAPRYLYL GLYCOL; 1,2-HEXANEDIOL; LINSEED OIL; EVENING PRIMROSE OIL; CHIA SEED OIL; ACAI OIL; TRISODIUM ETHYLENEDIAMINE DISUCCINATE; XANTHAN GUM; AMARANTHUS CAUDATUS SEED; VACHELLIA FARNESIANA WHOLE

Renove UV Shield Broad Spectrum SPF50

ACTIVE INGREDIENTS

Avobenzone 3%

Octinoxate 6.2%

PURPOSE

Sunscreen

USES

- helps prevent sunburn
- if used as directed with other sun protection measures (see Directions), decreases the risk of skin cancer and early skin aging caused by the sun

WARNINGS

- For external use only

Do not use on

damaged or broken skin

When using this product

keep out of eyes. Rinse with water to remove

Keep out of reach of children.

If swallowed, get medical help or contact a Poison Control Center right away.

DIRECTIONS

- Apply liberally 15 minutes before sun exposure.
- Reapply after 80 minutes of swimming or sweating.
- Immediately after towel drying
- At least every 2 hours
- Sun protection Measures. Spending time in the sun increases your risk of skin cancer and early skin aging. To decrease this risk, regularly use a sunscreen with a Broad Spectrum SPF value of 15 or higher and other sun protection measures including:

• Limit time in the sun, especially from 10 a.m.-2 p.m.

• Wear long-sleeved shirts, pants, hats, and sunglasses

- Children under 6 years of age: Ask a doctor.

INACTIVE INGREDIENTS

CARTHAMUS TINCTORIUS (SAFFLOWER) OLEOSOMES

DICAPRYLYL CARBONATE
FRAGARIA VESCA FRUIT

GLYCERIN

SUNFLOWER SEED

WATER
CAPRYLHYDROXAMIC ACID
CAPRYLYL GLYCOL

1,2-HEXANEDIOL
LINSEED OIL
EVENING PRIMROSE OIL
CHIA SEED OIL
ACAI OIL
TRISODIUM ETHYLENEDIAMINE DISUCCINATE
XANTHAN GUM
AMARANTHUS CAUDATUS SEED
VACHELLIA FARNESIANA WHOLE
ORANGE
GREEN TEA LEAF

Acrylates

Plankton Extract

OTHER INFORMATION

Protect this product from excessive heat and direct sun.